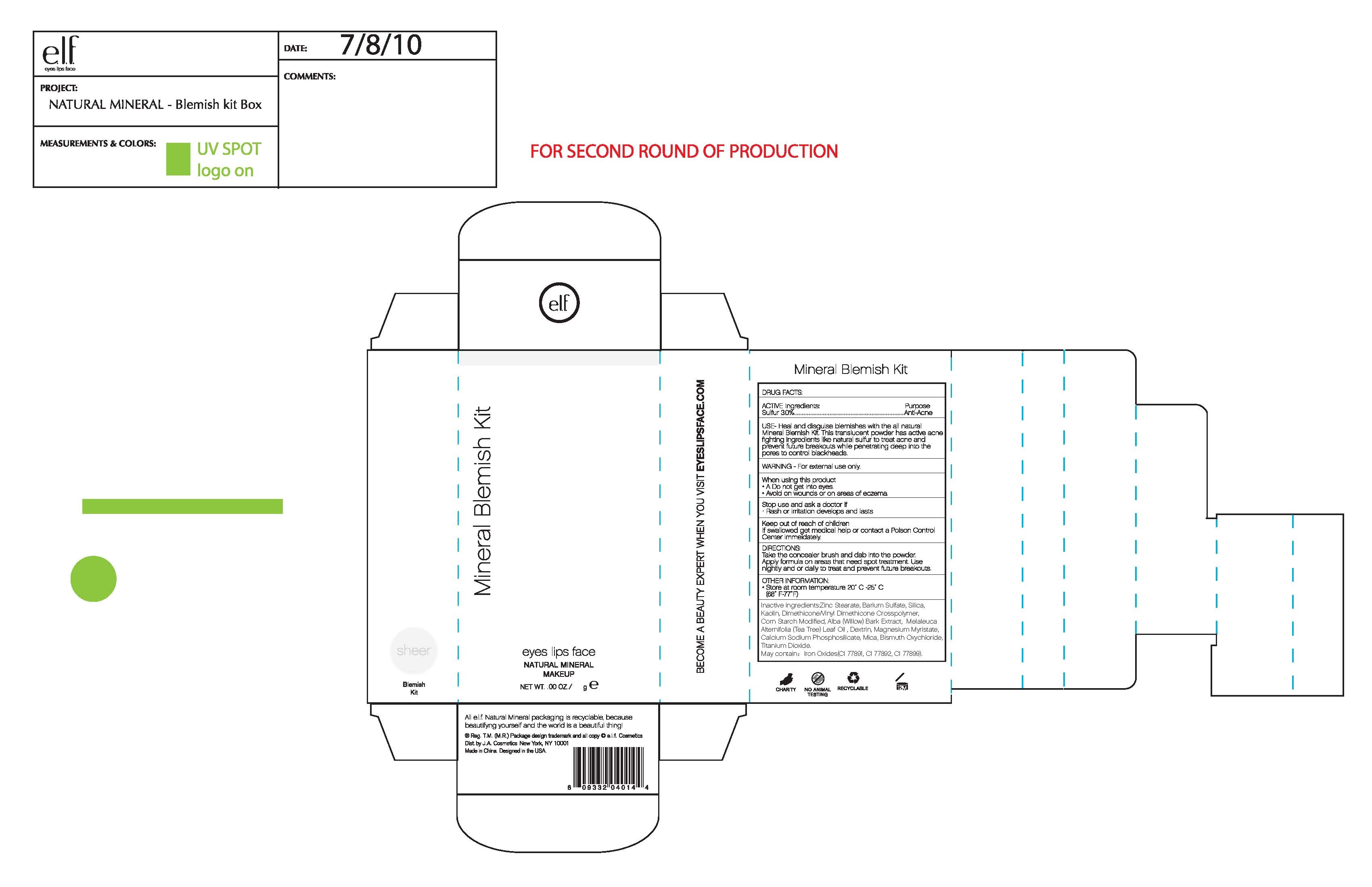 DRUG LABEL: ELFMineral Blemish Kit Box
NDC: 52664-006 | Form: POWDER
Manufacturer: Hangzhou Facecare Cosmetics Co., Ltd.
Category: otc | Type: HUMAN OTC DRUG LABEL
Date: 20101117

ACTIVE INGREDIENTS: SULFUR 3 g/100 g
INACTIVE INGREDIENTS: ZINC STEARATE 41.4 g/100 g; BARIUM SULFATE 35.0 g/100 g; SILICON DIOXIDE; KAOLIN; WILLOW BARK; TEA TREE OIL; FERRIC OXIDE RED; FERRIC OXIDE YELLOW; FERROSOFERRIC OXIDE; ALFADEX; MICA; BISMUTH OXYCHLORIDE; TITANIUM DIOXIDE

Drug Fact

Active Ingredient:

Sulfur 3.0%

Purpose:

Anti Acne

Uses:

Heal and disguise blemishes with the all natural Mineral Blemish Kit. This translucent powder has active acne fighting ingredients like nature sulfur to treat acne and prevent future breakouts while penetrate deep into the pores to control blackheads.

Warning:

For external use only

When Using This Product:

Do not get into eyes

Avoid on wounds and on areas of eczema

Stop Use and Ask A Doctor If:

Rash or irritation develops and lasts

Keep Out of Reach of Children:

If swallowed get medical help or contact a Poison Control Center immediately

Directions:

Take the concealer brush and dap into powder. Apply formula on areas that need spot treatment. Use nightly or daily to treat and prevent future breakouts.

Other Information:

Store at room temperature 20-25C (68-77F)

Inactive Ingredient:

Zince Stearate, Barium Sulfate, Silica, Kaolin, Dimethicone/Vinyl Dimethicone Crosspolymer, Corn Starch Modified, Alba (Willow) Bark Extract, Melaleuca Alternifolia (Tea Tree) Leaf Oil, Dextrin, Magnesium Myristate, Calcium Sodium Phosphosilicate, Mica, Bismuth Oxychloride, Titanium Dioxide

May contain:

Iron Oxides (CI 77491, CI 77492, CI 77499)

PACKAGE LABEL

labe